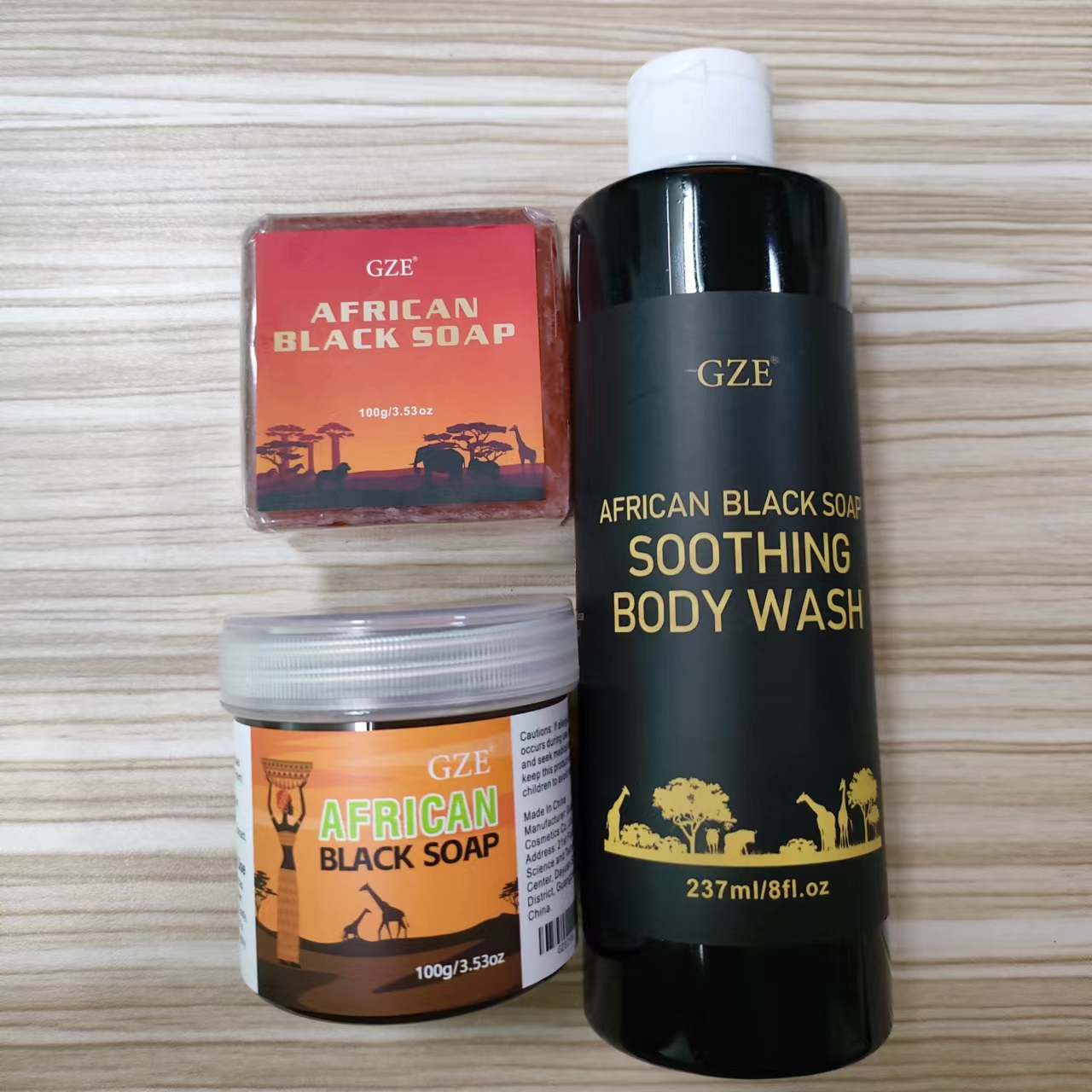 DRUG LABEL: GZE African Black SoapSet
NDC: 74458-313 | Form: KIT | Route: TOPICAL
Manufacturer: Guangzhou Yilong Cosmetics Co., Ltd
Category: otc | Type: HUMAN OTC DRUG LABEL
Date: 20241108

ACTIVE INGREDIENTS: SALICYLIC ACID 1.5 g/100 mL; BUTYROSPERMUM PARKII (SHEA) BUTTER 42.5 g/100 mL; BUTYROSPERMUM PARKII (SHEA) BUTTER 30 g/100 g; COCONUT OIL 5 g/100 g; ELAEIS GUINEENSIS (PALM) KERNEL OIL 30 g/100 g; BUTYROSPERMUM PARKII (SHEA) BUTTER 10 g/100 g; ELAEIS GUINEENSIS (PALM) KERNEL OIL 20 g/100 g; COCOS NUCIFERA (COCONUT) OIL 17 g/100 g; MUSA PARADISIACA (BANANA) FRUIT EXTRACT 10 g/100 g
INACTIVE INGREDIENTS: ELAEIS GUINEENSIS (PALM) OIL; CARICA PAPAYA (PAPAYA) FRUIT EXTRACT; MUSA PARADISIACA (BANANA) FRUIT EXTRACT; AQUA; COCOA SHELL; AQUA; TOCOPHEROL

GZE African Black Soap Set

ACTIVE INGREDIENT

Butyrospermum Parkii (Shea) Butter

Elaeis Guineensis (Palm) Kernel Oil

Cocos Nucifera (Coconut) Oil

Salicylic Acid

PURPOSE

Skin cleaning and care.

INACTIVE INGREDIENT

Aqua

Tocopherol

INDICATIONS AND USAGE

Cut a smaller bar size piece for use. Lather with a sponge,wash cloth,loofah, or similar device after getting it wet. Apply to any part of the body you want cleaned. Rinse & Repeat as desired.

WARNINGS

For external use only.

Stop use and ask a doctor if rash occurs.

Do not use on damaged or broken skin.

When using this product keep out of eyes. Rinse with water to remove.

Keep out of reach of children. If swallowed, get medical help or contact a Poison Control Center right away.

DOSAGE AND ADMINISTRATION

Cut a smaller bar size piece for use. Lather with a sponge,wash cloth,loofah, or similar device after getting it wet. Apply to any part of the body you want cleaned. Rinse & Repeat as desired.